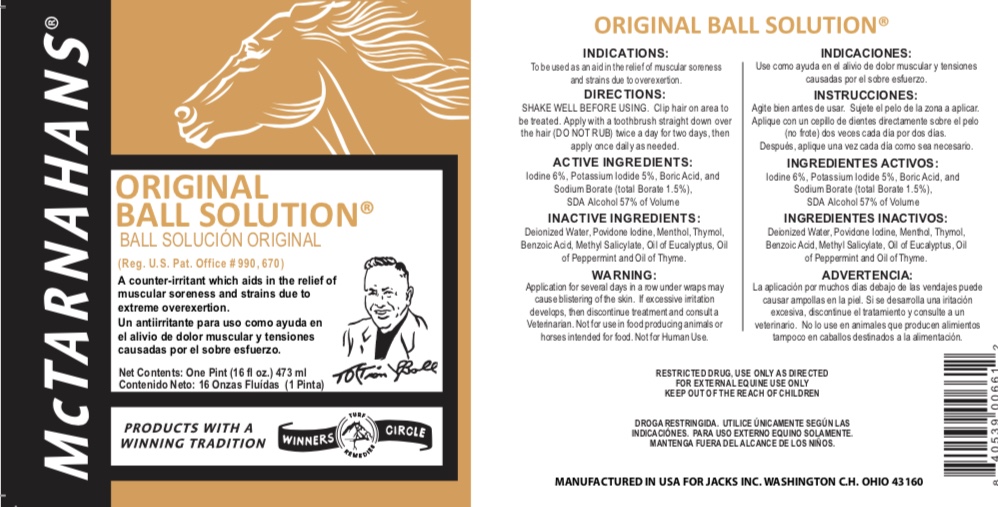 DRUG LABEL: Ball Solutions
NDC: 61156-100 | Form: LINIMENT
Manufacturer: JACKS MFG INC
Category: animal | Type: OTC ANIMAL DRUG LABEL
Date: 20211208

ACTIVE INGREDIENTS: ALCOHOL 0.57 mL/1 mL; IODINE 0.06 g/1 mL; POTASSIUM IODIDE 0.05 g/1 mL; BORIC ACID 0.01 g/1 mL; SODIUM BORATE 0.002 g/1 mL
INACTIVE INGREDIENTS: WATER 0.29 mL/1 mL; POVIDONE-IODINE 0.01 g/1 mL; BENZOIC ACID 0.001 g/1 mL; EUCALYPTOL 0.001 mL/1 mL; THYMOL 0.001 g/1 mL; THYME OIL 0.00015 mL/1 mL; PEPPERMINT OIL 0.00015 mL/1 mL; METHYL SALICYLATE 0.00015 mL/1 mL; MENTHOL 0.00005 g/1 mL

BALL SOLUTION

Indications

To be used as an aid in the relief of muscle soreness and strains due to overexertion.